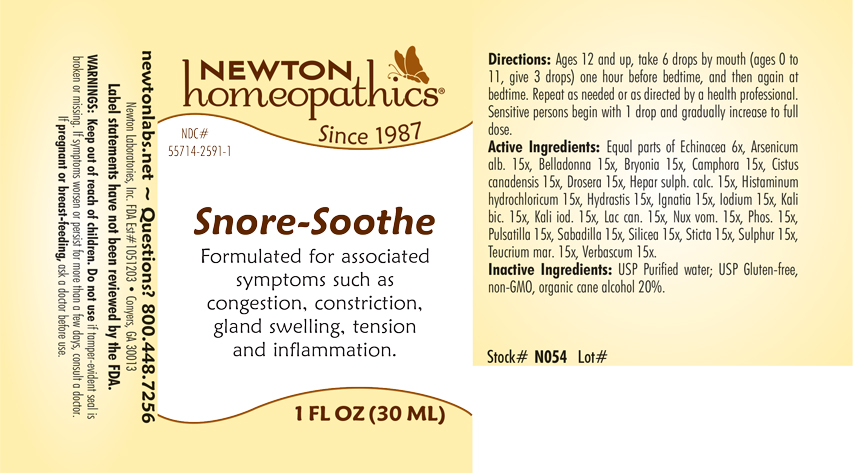 DRUG LABEL: Snore-Soothe
NDC: 55714-2591 | Form: LIQUID
Manufacturer: Newton Laboratories, Inc.
Category: homeopathic | Type: HUMAN OTC DRUG LABEL
Date: 20240319

ACTIVE INGREDIENTS: ECHINACEA, UNSPECIFIED 6 [hp_X]/1 mL; HELIANTHEMUM CANADENSE 15 [hp_X]/1 mL; DROSERA ANGLICA 15 [hp_X]/1 mL; CALCIUM SULFIDE 15 [hp_X]/1 mL; GOLDENSEAL 15 [hp_X]/1 mL; STRYCHNOS IGNATII SEED 15 [hp_X]/1 mL; IODINE 15 [hp_X]/1 mL; POTASSIUM DICHROMATE 15 [hp_X]/1 mL; POTASSIUM IODIDE 15 [hp_X]/1 mL; PHOSPHORUS 15 [hp_X]/1 mL; ANEMONE PULSATILLA 15 [hp_X]/1 mL; SCHOENOCAULON OFFICINALE SEED 15 [hp_X]/1 mL; SILICON DIOXIDE 15 [hp_X]/1 mL; LOBARIA PULMONARIA 15 [hp_X]/1 mL; SULFUR 15 [hp_X]/1 mL; TEUCRIUM MARUM 15 [hp_X]/1 mL; VERBASCUM THAPSUS 15 [hp_X]/1 mL; ARSENIC TRIOXIDE 15 [hp_X]/1 mL; ATROPA BELLADONNA 15 [hp_X]/1 mL; HISTAMINE DIHYDROCHLORIDE 15 [hp_X]/1 mL; CANIS LUPUS FAMILIARIS MILK 15 [hp_X]/1 mL; STRYCHNOS NUX-VOMICA SEED 15 [hp_X]/1 mL; BRYONIA ALBA ROOT 15 [hp_X]/1 mL; CAMPHOR (NATURAL) 15 [hp_X]/1 mL
INACTIVE INGREDIENTS: ALCOHOL; WATER

Snore 2591L

INDICATIONS & USAGE SECTION

Formulated for associated symptoms such as congestion, constriction, gland swelling, tension and inflammation.

DOSAGE & ADMINISTRATION SECTION

Directions: Ages 12 and up, take 6 drops by mouth (ages 0 to 11, give 3 drops) one hour before bedtime, and then again at bedtime. Repeat as needed or as directed by a health professional. Sensitive persons begin with 1 drop and gradually increase to full dose.

OTC - ACTIVE INGREDIENT SECTION

Equal parts of Echinacea 6x, Arsenicum alb. 15x, Belladonna 15x, Bryonia 15x, Camphora 15x, Cistus canadensis 15x, Drosera 15x, Hepar sulph. calc. 15x, Histaminum hydrochloricum 15x, Hydrastis 15x, Ignatia 15x, Iodium 15x, Kali bic. 15x, Kali iod. 15x, Lac can. 15x, Nux vom. 15x, Phos. 15x, Pulsatilla 15x, Sabadilla 15x, Silicea 15x, Sticta 15x, Sulphur 15x, Teucrium mar. 15x, Verbascum 15x.

OTC - PURPOSE SECTION

Formulated for associated symptoms such as congestion, constriction, gland swelling, tension and inflammation.

INACTIVE INGREDIENT SECTION

Inactive Ingredients: USP Purified Water; USP Gluten-free, non-GMO, organic cane alcohol 20%

QUESTIONS SECTION

newtonlabs.net - Questions? 800.448.7256

Newton Laboratories, Inc. FDA Est # 1051203 Conyers, GA 30013

WARNINGS SECTION

WARNINGS: Keep out of reach of children. Do not use if tamper-evident seal is broken or missing. If symptoms worsen or persist for more than a few days, consult a doctor. If pregnant or breast-feeding, ask a doctor before use.

OTC - PREGNANCY OR BREAST FEEDING SECTION

If pregnant or breast-feeding, ask a doctor before use.

OTC - KEEP OUT OF REACH OF CHILDREN SECTION

Keep out of reach of children.